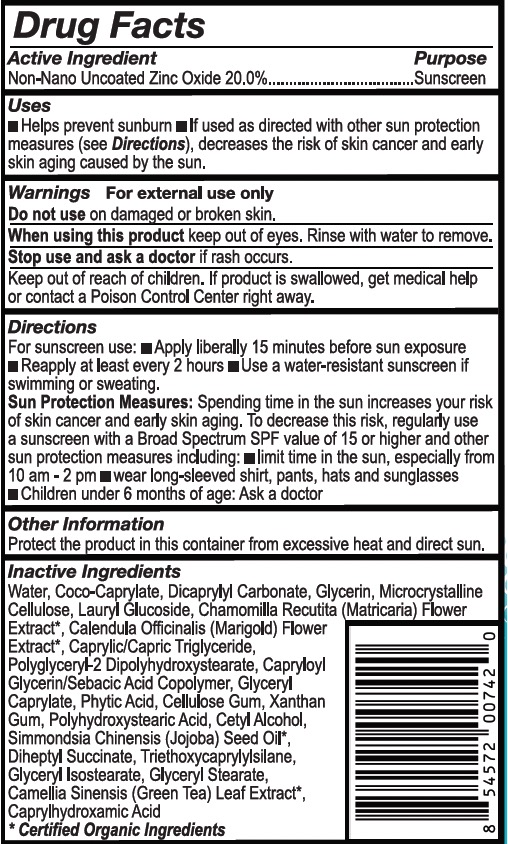 DRUG LABEL: Fresh Monster Mineral Sunscreen
NDC: 84792-120 | Form: LOTION
Manufacturer: Blue Zebra Brands, Inc.
Category: otc | Type: HUMAN OTC DRUG LABEL
Date: 20241119

ACTIVE INGREDIENTS: ZINC OXIDE 0.6 g/3 g
INACTIVE INGREDIENTS: COCO-CAPRYLATE

USES

- Helps prevent sunburn
- If used as directed with other sun protection measures (see Directions), decreases the risk of skin cancer and early skin aging caused by the sun.

WARNINGS

For External Use Only

Do not use on damaged or broken skin

When using this product keep out of eyes. Rinse with water to remove.

Stop use and ask a doctor if rash occurs.

Keep out of reach of children. If product is swallowed, get medical help or contact a Poison Control Center right away.

DIRECTIONS

For sunscreen use:

- Apply liberally 15 minutes before sun exposure
- Reapply at least every 2 hours
- Use a water-resistant sunscreen if swimming or sweating.

Sun Protection Measures

Spending time in the sun increases your risk of skin cancer and early skin aging. To decrease this risk, regularly use a sunscreen with a Broad Spectrum SPF value of 15 or higher and other sun protection measures including:

- limit time in the sun, especially from 10am -2pm
- wear long-sleeved shirt, pants, hats and sunglasses

Children under 6 months of age: Ask a doctor

INACTIVE INGREDIENTS:

Water, Coco-Caprylate, Dicaprylyl Carbonate, Glycerin, Microcrystalline Cellulose, Lauryl Glucoside, Chamomilla Recutita (Matricaria) Flower Extract*, Calendula Officinalis (Marigold) Flower Extract*, Caprylic/Capric Triglyceride, Polyglyceryl-2 Dipolyhydroxystearate, Capryloyl Glycerin/Sebacic Acid Copolymer, Glyceryl Caprylate, Phytic Acid, Cellulose Gum, Xanthan Gum, Polyhydroxystearic Acid, Cetyl Alcohol, Simmondsia Chinensis (Jojoba) Seed Oil*, Diheptyl Succinate, Triethoxycaprylylsilane, Glyceryl Isostearate, Glyceryl Stearate, Camellia Sinensis (Green Tea) Leaf Extract*, Caprylhydroxamic Acid.

*Certified Organic Ingredients

PACKAGE LABEL

Non-Nano Uncoated Zinc Oxide 20.0%